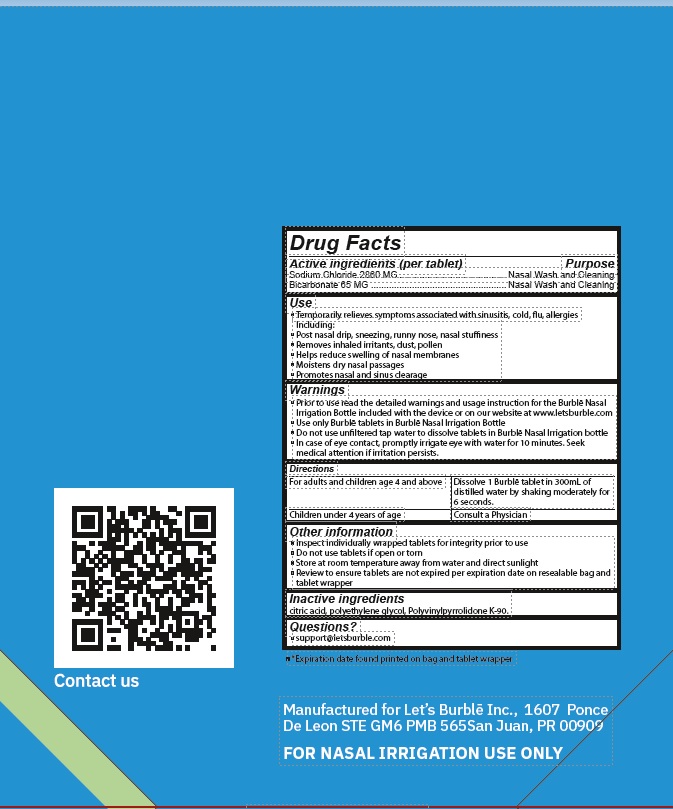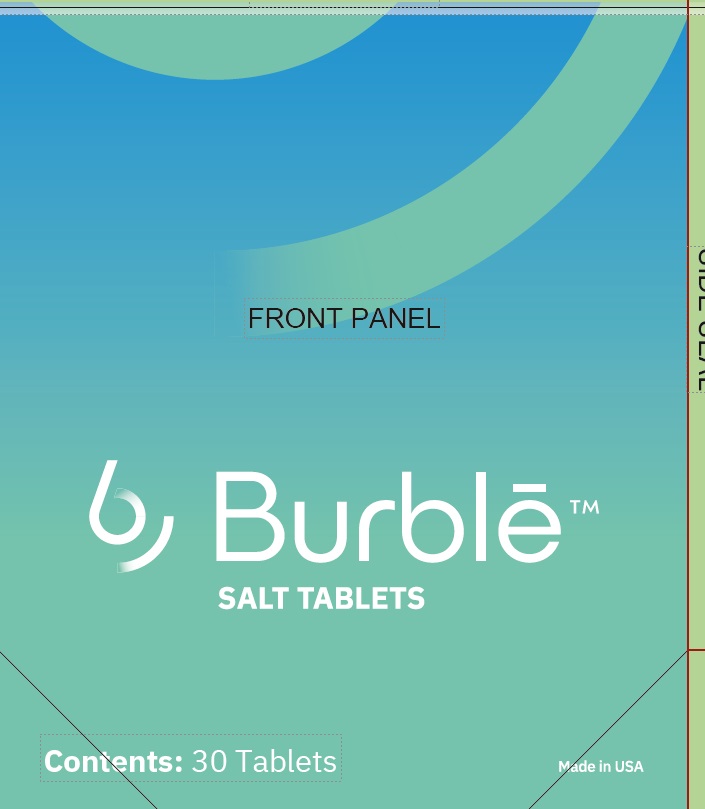 DRUG LABEL: BURBLE
NDC: 83557-001 | Form: TABLET, FOR SOLUTION
Manufacturer: LETS BURBLE, INC.
Category: otc | Type: HUMAN OTC DRUG LABEL
Date: 20251227

ACTIVE INGREDIENTS: SODIUM CHLORIDE 2860 mg/1 1; CALCIUM BICARBONATE 65 mg/1 1
INACTIVE INGREDIENTS: ANHYDROUS CITRIC ACID; POVIDONE K90; POLYETHYLENE GLYCOL 8000

Burble Salt Tablets, 30ct (83557-001-30)

Active Ingredients

Sodium Chloride 2860 MG .......................................... Nasal Wash and Cleaning
Bicarbonate 65 MG ..................................................... Nasal Wash and Cleaning

Use

Temporarily relieves symptons associated with sinusitis, cold, flu, allergies
Including:

- Post nasal drip, sneezing, runny nose, nasal stuffiness
- Removes inhaled irritants, dust, pollen
- Helps reduce swelling of nasal membranes
- Moistens dry nasal passages
- Promotes nasal and sinus clearage

Warnings

- Prior to use read the detailed warnings and usage instruction for the Burble Nasal Irrigation Bottle included with the device or on our website at www.letsburble.com
- Use only Burble tablets in Burble Nasal Irrigation Bottle
- Do not use unfiltered tap water to dissolve tablets in Burble Nasal Irrigation bottle

Do not use tablets if open or torn

STOP USE

In case of eye contact, promptly irrigate eye with water for 10 minutes. Seek medical attention if irritation persists.

Keep out out of reach of children

Consult a Physician

Other Infomation

- Inspect individually wrapped tablets for integrity prior to use
- Do not use tablets if open or torn
- Store at room temperature away from water and direct sunlight
- Review to ensure tablets are not expired per expiration date on resealable bag and tablet wrapper

Directions

For adults and children age 4 and above Dissolve 1 Burble tablet in 300mL of distilled water by shaking moderately for 6 seconds.
Children under 4 years of age Consult a Physician

Inactive Ingredients

citric acid, polyethylene glycol, Polyvinylpyrrolidone K-90

Questions?

support@letsburble.com

Manufactured for Let’s Burble Inc., 1607 Ponce
De Leon STE GM6 PMB 565San Juan, PR 00909
FOR NASAL IRRIGATION USE ONLY

PDP

Burble Salt Tablets (83557-001-30)